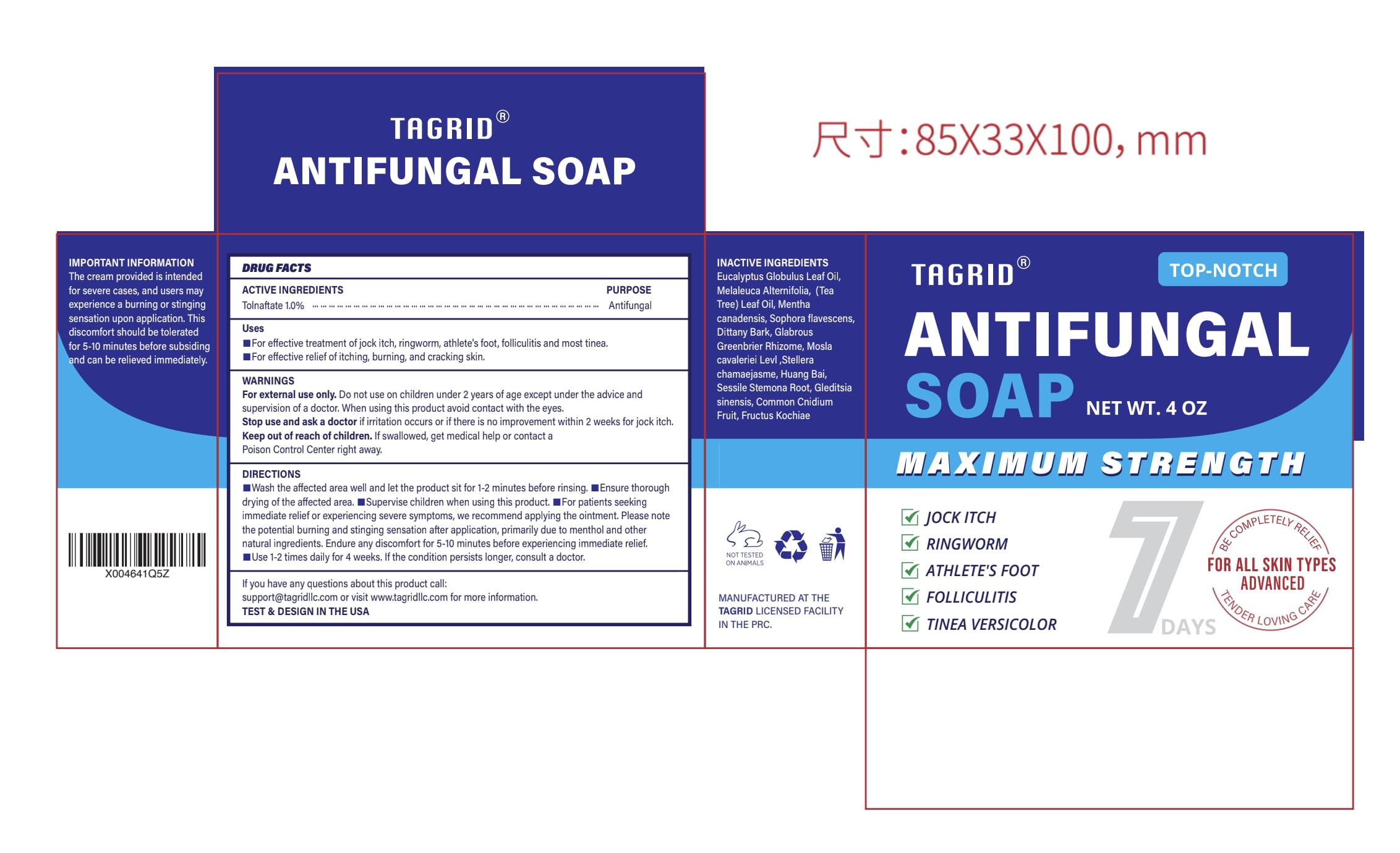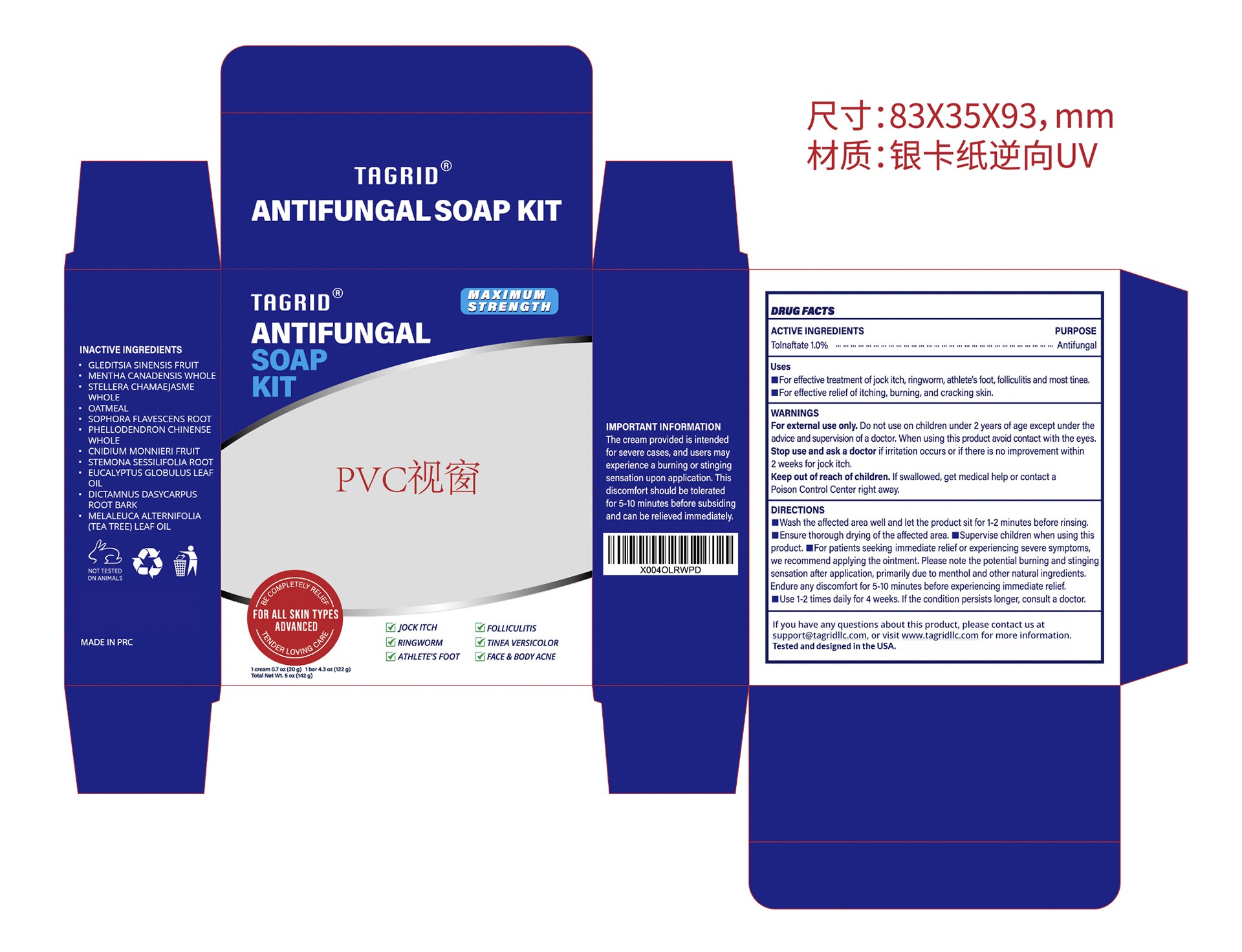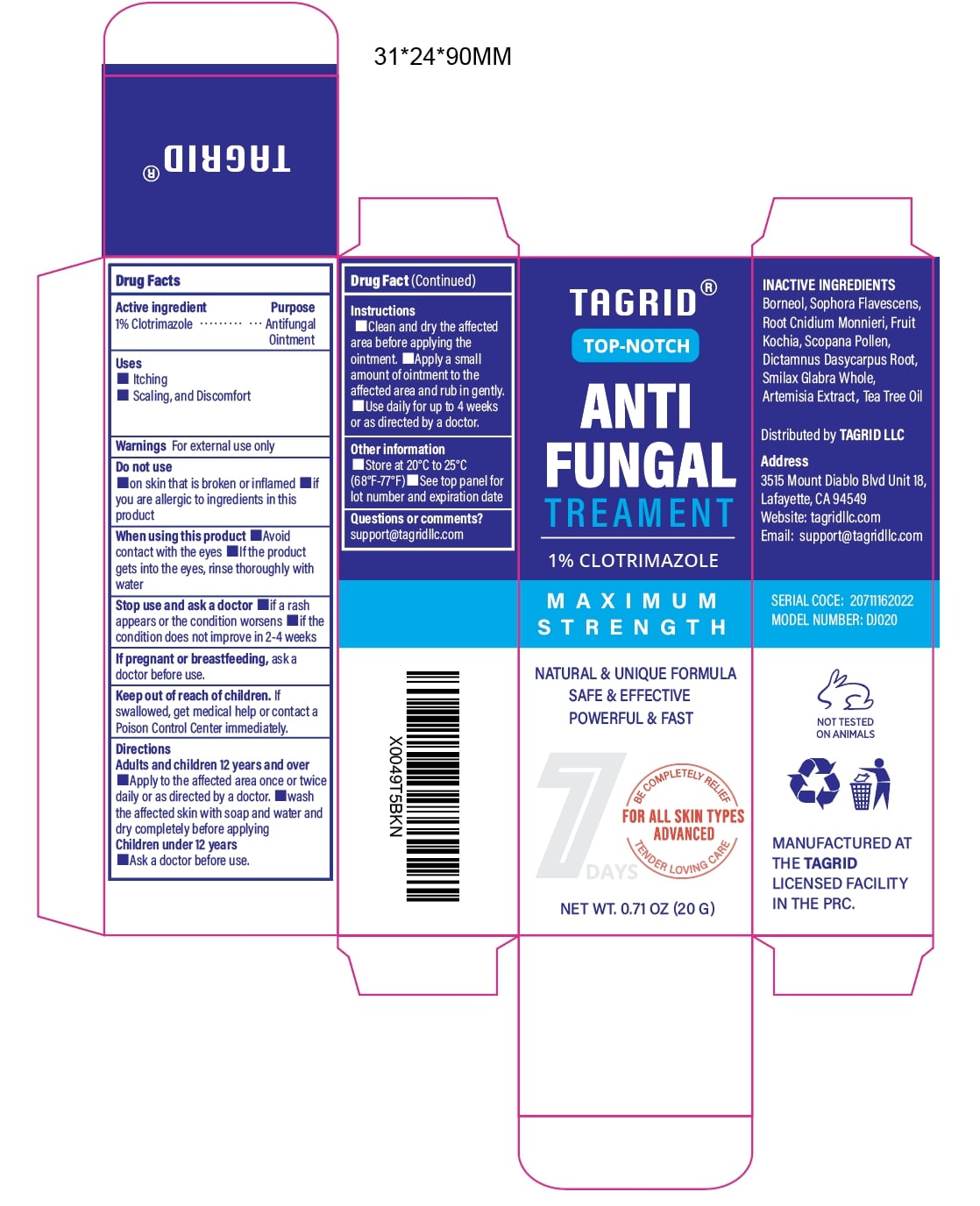 DRUG LABEL: Tagrid Antifungal Kit
NDC: 85384-0014 | Form: KIT | Route: TOPICAL
Manufacturer: TAGRID LLC
Category: otc | Type: HUMAN OTC DRUG LABEL
Date: 20250609

ACTIVE INGREDIENTS: TOLNAFTATE 10 mg/1 g; Clotrimazole 10 mg/1 g
INACTIVE INGREDIENTS: GLEDITSIA SINENSIS FRUIT; MENTHA CANADENSIS WHOLE; STELLERA CHAMAEJASME WHOLE; OATMEAL; SOPHORA FLAVESCENS ROOT; PHELLODENDRON CHINENSE WHOLE; CNIDIUM MONNIERI FRUIT; STEMONA SESSILIFOLIA ROOT; EUCALYPTUS GLOBULUS LEAF OIL; DICTAMNUS DASYCARPUS ROOT BARK; MELALEUCA ALTERNIFOLIA (TEA TREE) LEAF OIL; CNIDIUM MONNIERI FRUIT; DICTAMNUS DASYCARPUS ROOT BARK; TEA TREE OIL; BORNEOL; BASSIA SCOPARIA POLLEN; SOPHORA FLAVESCENS ROOT; BASSIA SCOPARIA FRUIT; ARTEMISIA ARGYI LEAF; SMILAX GLABRA WHOLE

Initial Drug Listing - Tagrid Antifungal Kit (Soap + Cream)

DESCRIPTION

Tagrid Antifungal Kit (Soap + Cream)

This package contains:

- One bar of antifungal soap with Tolnaftate and herbal ingredients.
- One tube of antifungal cream with Clotrimazole 1% for enhanced relief.

See product labeling below for full directions and warnings. Main instructions on this box are based on soap usage. See cream label for specific use cases.

Questions? Contact support@tagridllc.com or visit www.tagridllc.com

ACTIVE INGREDIENT

Tolnaftate

INDICATIONS AND USAGE

- For effective treatment of jock itch, ringworm, athlete's foot, and folliculitis tinea.
- For effective relief of itching, burning, and cracking skin.

WARNINGS

For external use only

Do not use on children under 2 years of age exceptunder the advice and supervision of a doctor.

When using this product avoid contact with the eyes.

Stop use and ask a doctor if irritation occurs or if there is no improvement within 2weeks for jock itch.

Keep out of reach of children. If swallowed, get medical help or contact a Poison Control Center right away.

DIRECTIONS

- Wash the affected area well and let the product sit for 1-2 minutes before rinsing.
- Ensure thorough drying of the affected area.
- Supervise children when using this product.
- For patients seeking immediate relief or experiencing severe symptoms, we recommend applying the ointment.
- Please note the potential burning and stinging sensation after application, primarily due to menthol and other natural ingredients.
- Endure any discomfort for 5-10 minutes before experiencing immediate relief.
- Use 1-2 times daily for 4 weeks. If the condition persists longer, consult a doctor.

OTHER SAFETY INFORMATION

- The cream provided is intended for severe cases.
- Users may experience a burning or stinging sensation upon application.
- This discomfort should be tolerated for 5–10 minutes before subsiding and can be relieved immediately.

QUESTIONS

If you have any questions about this product, please contact us at support@tagridllc.com, or visit www.tagridllc.com for more information.
Tested and designed in the USA.

INACTIVE INGREDIENT

Ingredients:

- GLEDITSIA SINENSIS FRUIT
- MENTHA CANADENSIS WH LE
- STELLERA CHAMAEJASME WHOLE
- OATMEAL
- SOPHORA FLAVESCENS ROOT
- PHELLODENDRON CHINENSE WHOLE
- CNIDIUM MONNIERI FRUIT
- STEMONA SESSILIFOLIA ROOT
- EUCALYPTUS GLOBULUS LEAF OIL
- DICTAMNUS DASYCARPUS ROOT BARK
- MELALEUCA ALTERNIFOLIA (TEA TREE) LEAF OIL

ACTIVE INGREDIENT

Clotrimazole 1%

PURPOSE

Antifungal Ointment

INDICATIONS AND USAGE

- Treats fungal infections of the skin, such as folliculitis, athlete's foot, jock itch, ringworm, and seborrheic dermatitis.
- Effective for relieving symptoms of itching, scaling, redness, and discomfort caused by fungal infections.
- Helps reduce and control fungal skin infections, including:
  - tinea corporis (body fungus)
  - tinea cruris (groin fungus)
  - tinea pedis (foot fungus)
  - tinea versicolor
- Can be used on areas prone to fungal growth, such as the scalp, face, chest, back, arms, and legs.

WARNINGS

For external use only.

DO NOT USE

on broken, inflamed, or severely irritated skin.

lf you are allergic to Clotrimazole or any other ingredients in this product.

WHEN USING

Avoid contact with the eyes. If the product gets into the eyes, rinse thoroughly with water.

Stop use and ask a doctor if: a rash appears. the condition does not improve within 2-4 weeks of regular use.

PREGNANCY OR BREAST FEEDING

ask a healthcare provider before use.

KEEP OUT OF REACH OF CHILDREN

If swallowed, get medical help or contact a Poison Control Center right away.

Directions

1. Adults and children 12 years and over:
  - Clean and dry the affected area before application.
  - Apply a small amount to the affected area once or twice daily, or as directed by a doctor.
  - Use continuously for up to 4 weeks, or as directed by a healthcare provider.
2. Children under 12 years:
  - Ask a doctor before use.

INSTRUCTIONS FOR USE

1. Clean the affected area thoroughly with soap and water and dry completely before applying the cream.
2. Apply a small amount of ointment to the affected area and gently rub in.
3. Use daily for up to 4 weeks, or as directed by a healthcare provider.

OTHER SAFETY INFORMATION

store at 20°C to 25°C (68°F-77°F).
see the top panel for lot number and expiration date.

Questions or comments?
Contact us at: support@tagridllc.com

INACTIVE INGREDIENT

- Borneol
- Sophora Flavescens Root
- Cnidium monnieri Root
- Bassia scoparia Fruit
- Scoparia Pollen
- Dictamnus Dasycarpus Root
- Smilax Glabra Whole
- Artemisia argyi Leaf
- Tea Tree Oil